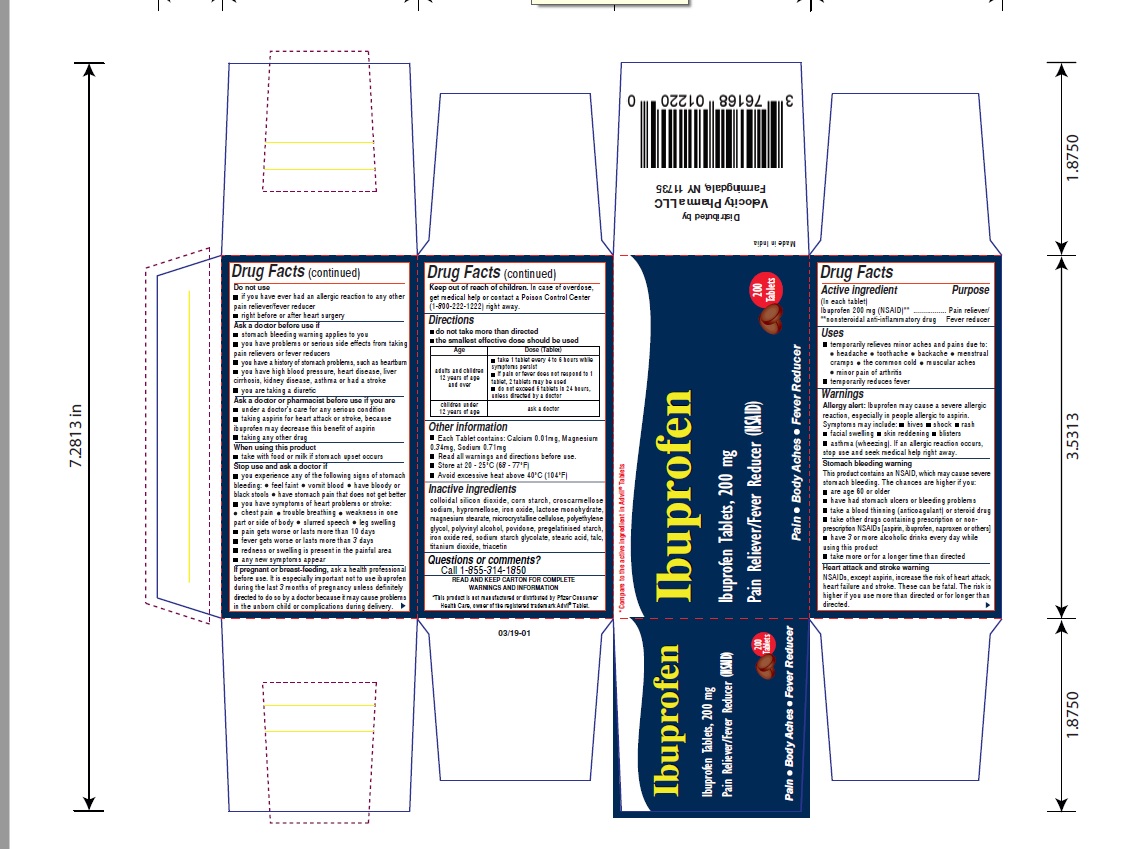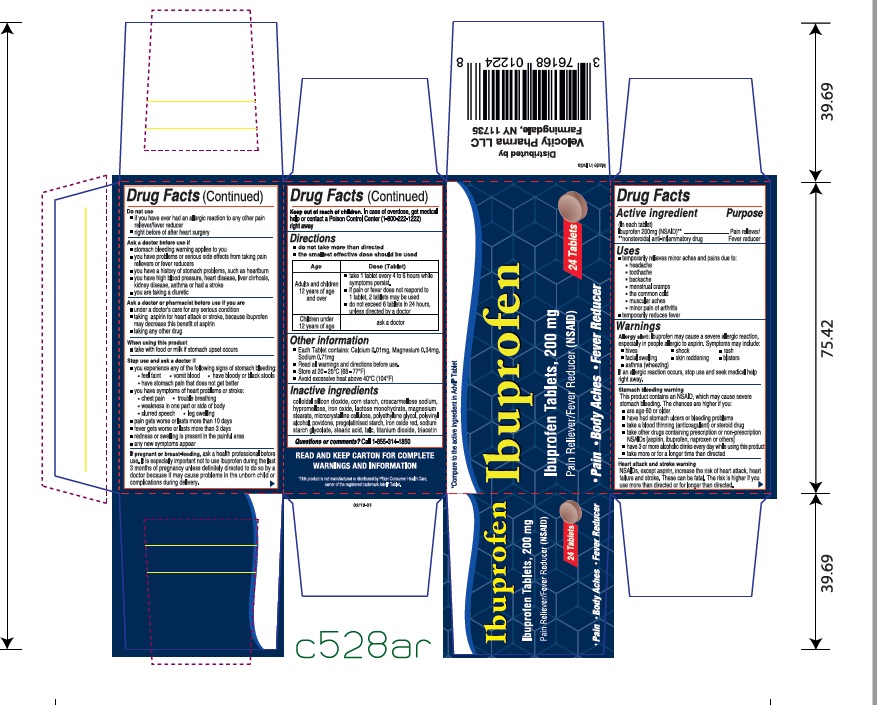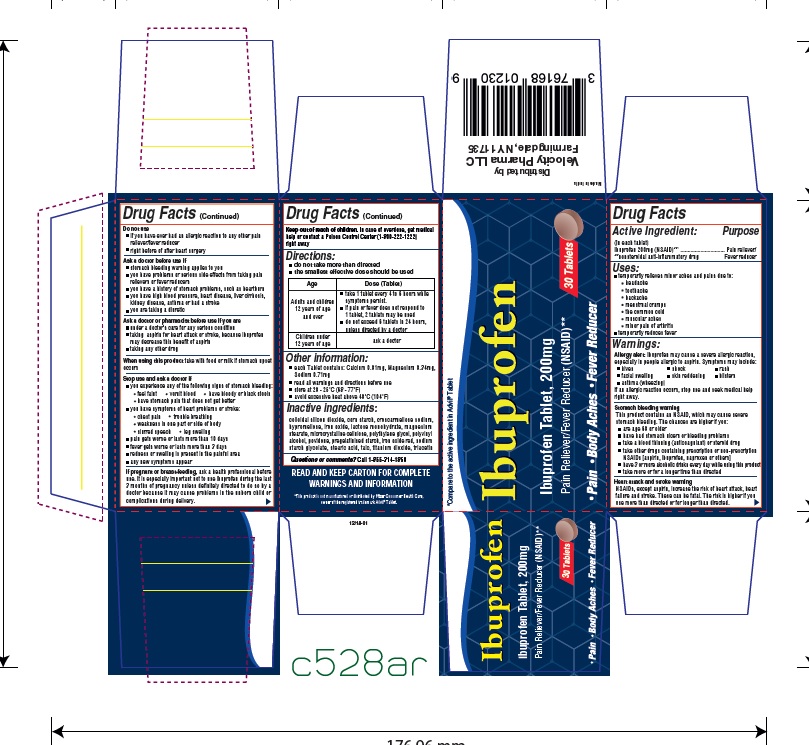 DRUG LABEL: Ibuprofen
NDC: 76168-095 | Form: TABLET, COATED
Manufacturer: Velocity Pharma
Category: otc | Type: HUMAN OTC DRUG LABEL
Date: 20190327

ACTIVE INGREDIENTS: IBUPROFEN 200 mg/1 1
INACTIVE INGREDIENTS: SILICON DIOXIDE; CROSCARMELLOSE SODIUM; FERRIC OXIDE RED; MAGNESIUM STEARATE; CELLULOSE, MICROCRYSTALLINE; POLYETHYLENE GLYCOL 1500; POLYVINYL ALCOHOL; STARCH, CORN; TALC; TITANIUM DIOXIDE

Ibuprofen Tablets, USP 200mg

Active Ingredient

(in each tablet)

Ibuprofen 200 mg (NSAID)*

* nonsteroidal anti-inflammatory drug

Purpose

pain reliever/fever reducer

Uses

- temporarily relieves minor aches and pains due to:
- headache
- toothache
- backache
- menstrual cramps
- minor pains of arthritis
- muscular aches
- the common cold
- temporarily reduces fever

Warnings

Allergy alert: This product may cause a severe allergic reaction, especially in people allergic to aspirin, symptoms may include

- hives
- facial swelling
- asthma(wheezing)
- shock
- skin reddning
- rash
- blisters

if an allergic reaction occurs, stop use and seek medical help right away

Stomach bleeding warning: this product contains an NSAID, which may cause severe stomach bleeding. The chance is higher if you

- are age 60 or older
- have had stomach ulcers or bleeding problems
- take a blood thinning(anticoagulant) or steroid drug.
- take other drugs containing prescription or nonprescription NSAIDs [aspirin, ibuprofen, naproxen or others]
- have 3 or more alcoholic drinks every day while using this product
- take more or for a longer time than directed.

do not use

- this product if you have ever had an allergic reaction to any pain reliever/fever reducer
- right before or after heart surgery

ask your doctor before use if

- stomach bleeding warning applies to you
- you have problems or serious side effects from taking pain relievers or fever reducers
- you have a history of stomach problems such as heartburn
- you have high blood pressure, heart disease, liver cirrhosis, kidney disease or asthma

ask your doctor or pharmacist before use if you are

- under a doctor’s care for any serious condition
- taking aspirin for heart attack or stroke, because ibuprofen may decrease the benefit of aspirin
- taking any other drug

when using this product

- take with food or milk
- The risk of heart attack or stroke may increase if you are more than directed or for longer than directed

Stop use and ask a doctor if:

- you experience and of the following signs of stomach bleeding:
- feel faint
- vomit blood
- have bloody or black stools
- have stomach pain that does not get better
- pain gets worse or lasts more than 10 days
- fever gets worse or lasts more than 3 days
- redness or swelling is present in the painful area
- any new symptoms appear

If pregnant or breast-feeding, ask a health professional before use. it is especially important not to use ibuprofen during the last 3 months of pregnancy unless definitely directed by a doctor because it may cause problems in the unborn child or complications during delivery.

Keep out of reach of children.

In case of overdose, get medical help or contact a Poison Control Center right away.

Directions

- do not take more than directed
- the smallest effective dose should be used
- adults and children 12 years and over: take 1 tablet every 4 to 6 hours while symptoms persists.
- If pain or fever does not respond to 1 tablet, 2 tablets may be used
- do not exceed 6 tablets in 24 hours, unless directed by a doctor
- children under 12 years: ask a doctor

Other Information

- read all warnings and directions before use. keep carton
- store at 20-25 °C (68-77 °F)
- avoid excessive heat above 40°C (104°F)
- do not use if imprinted safety seal under the cap is broken or missing

Inactive Ingredients

Colloidal silicon Dioxide, corn starch, Croscarmellose Sodium, hypermellose, Iron Oxide red, lactose monohydrate, Magnesium Stearate, Microcrystalline Cellulose, Polyethylene Glycol, Polyvinyl Alcohol, povidone, Pregelatinized Starch, stearic acid, Talc, Titanium Dioxide, triacetin

Questions or Comments

Call toll free 1-855-314-1850